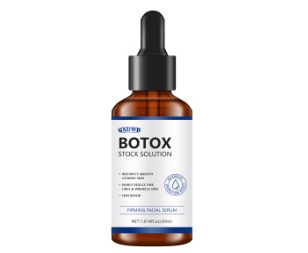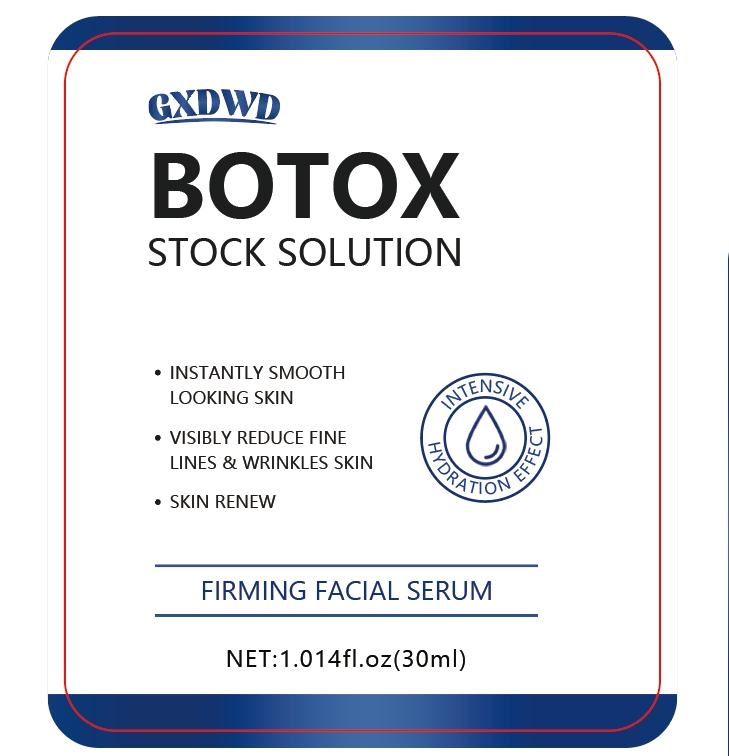 DRUG LABEL: facial essence
NDC: 84025-170 | Form: LOTION
Manufacturer: Guangzhou Yanxi Biotechnology Co.. Ltd
Category: otc | Type: HUMAN OTC DRUG LABEL
Date: 20240827

ACTIVE INGREDIENTS: CETEARYL OLIVATE 3 mg/30 mL; NIACINAMIDE 5 mg/30 mL
INACTIVE INGREDIENTS: WATER

DOSAGE AND ADMINISTRATION

For keeping skin translucent, moisturizing and firming skin

WARNINGS

keep out of children

INACTIVE INGREDIENT

AQUA

INDICATIONS AND USAGE

for daily skin care

keep out of children

PURPOSE

Effectively reduce skin fine lines and delay skin aging